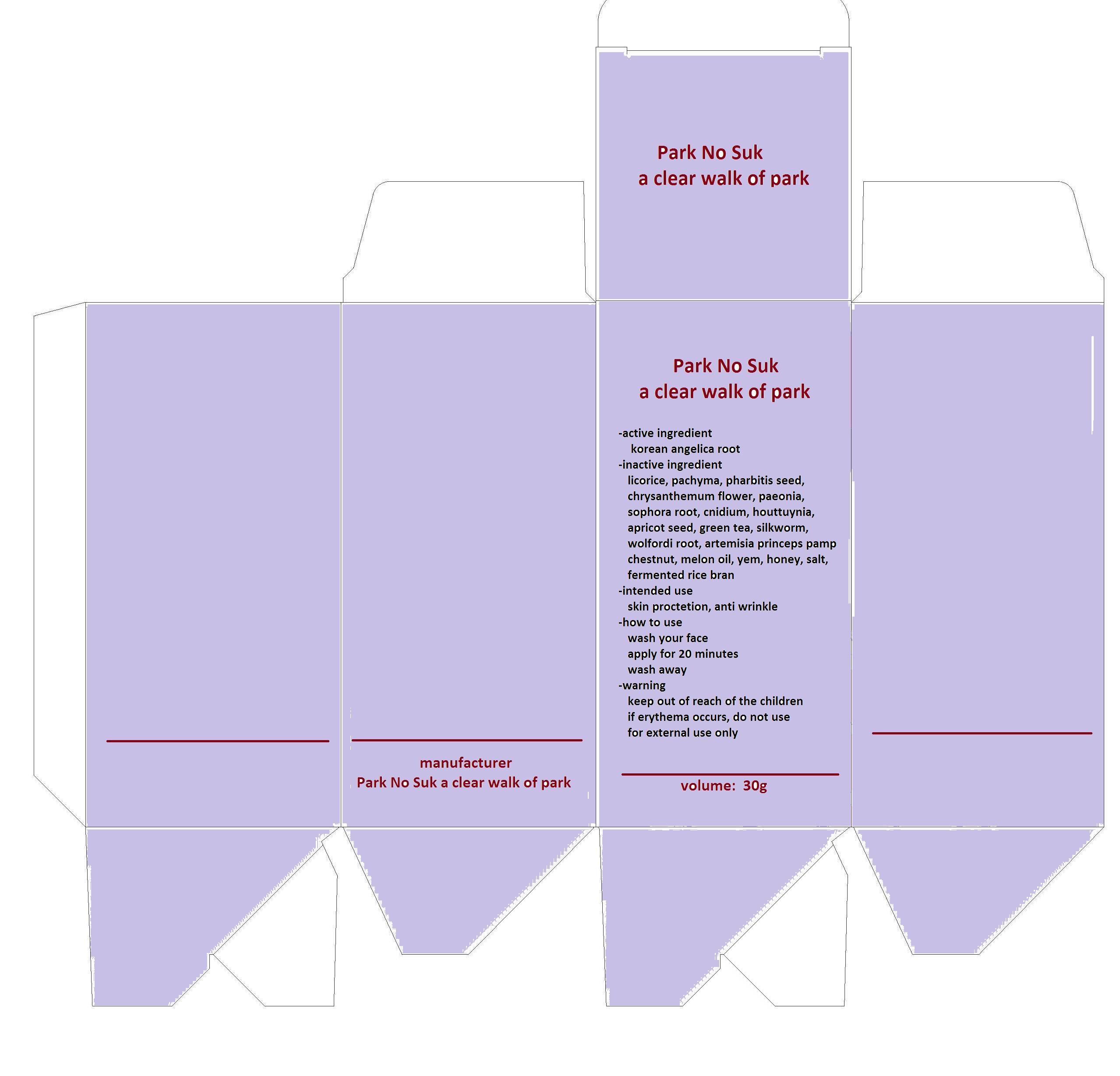 DRUG LABEL: Park no suk a clear walk of park
NDC: 55496-1001 | Form: CREAM
Manufacturer: Park No Suk a clear walk of park
Category: otc | Type: HUMAN OTC DRUG LABEL
Date: 20130306

ACTIVE INGREDIENTS: ANGELICA ARCHANGELICA ROOT 5 g/100 g
INACTIVE INGREDIENTS: GLYCYRRHIZA GLABRA; FU LING; IPOMOEA PURPUREA SEED; TANACETUM CINERARIIFOLIUM FLOWER; PAEONIA LACTIFLORA ROOT; SOPHORA FLAVESCENS ROOT; CNIDIUM MONNIERI FRUIT; HOUTTUYNIA CORDATA FLOWERING TOP; PASSIFLORA INCARNATA SEED; GREEN TEA LEAF; BOMBYX MORI FIBER; TRIPTERYGIUM WILFORDII ROOT; ARTEMISIA PRINCEPS LEAF; CHINESE CHESTNUT

Drug Facts

ACTIVE INGREDIENT

korea angelica root

INACTIVE INGREDIENT

licorice, pachyma, pharbitis seed, chrysanthemum flower, paeonia, sophora root, cnidium, houttuynia, apricot seed, green tea, silkworm, wolfordi root, artemisia princeps pamp, chestnut, melon oil, yem, honey, salt, fermented rice bran

PURPOSE

skin protection

keep out of reach of the children

INDICATIONS AND USAGE

- wash your face
- apply for 20 minutes
- wash away

WARNINGS

- if erythema occurs, do not use immediately

DOSAGE AND ADMINISTRATION

for external use only